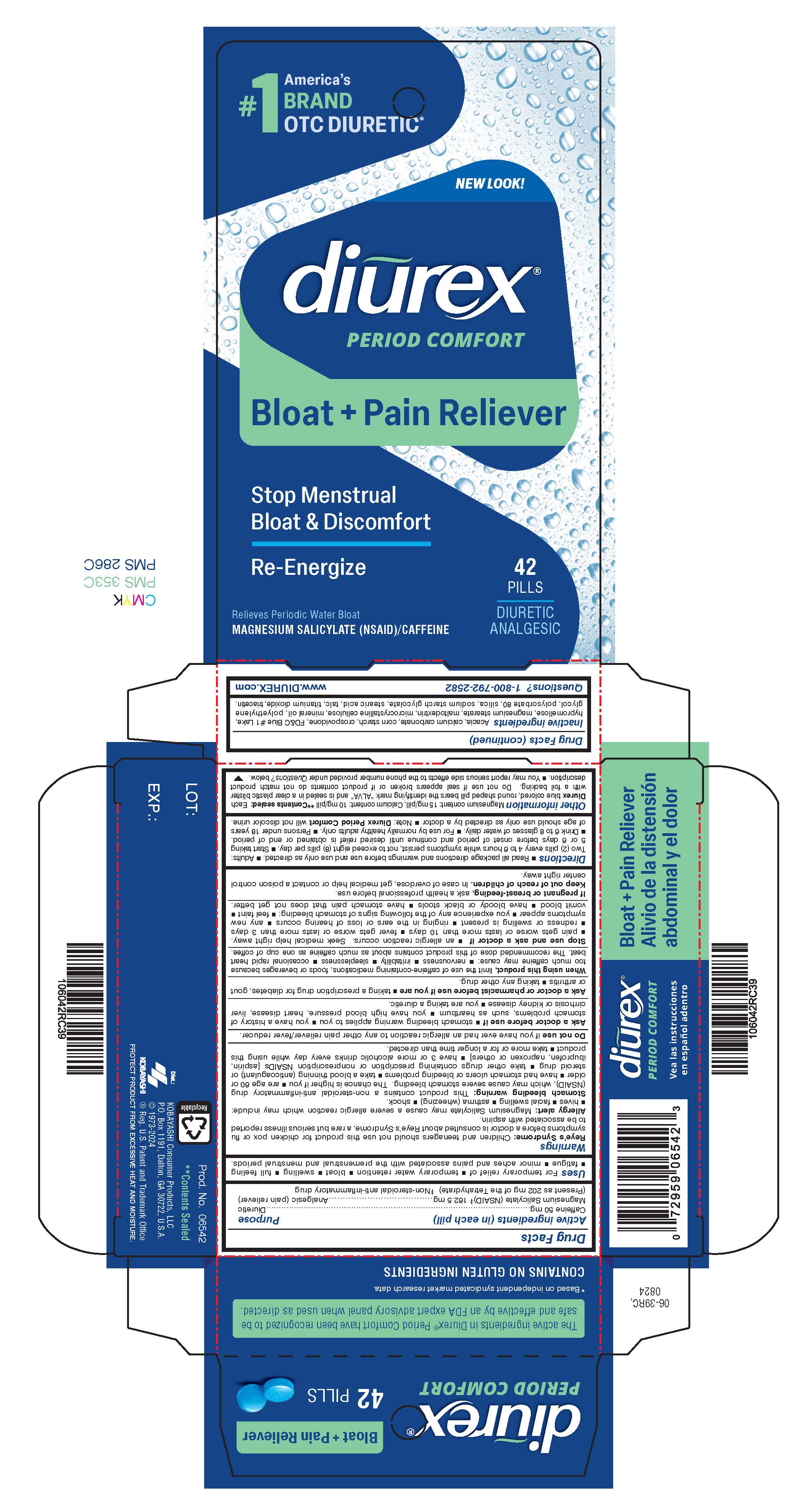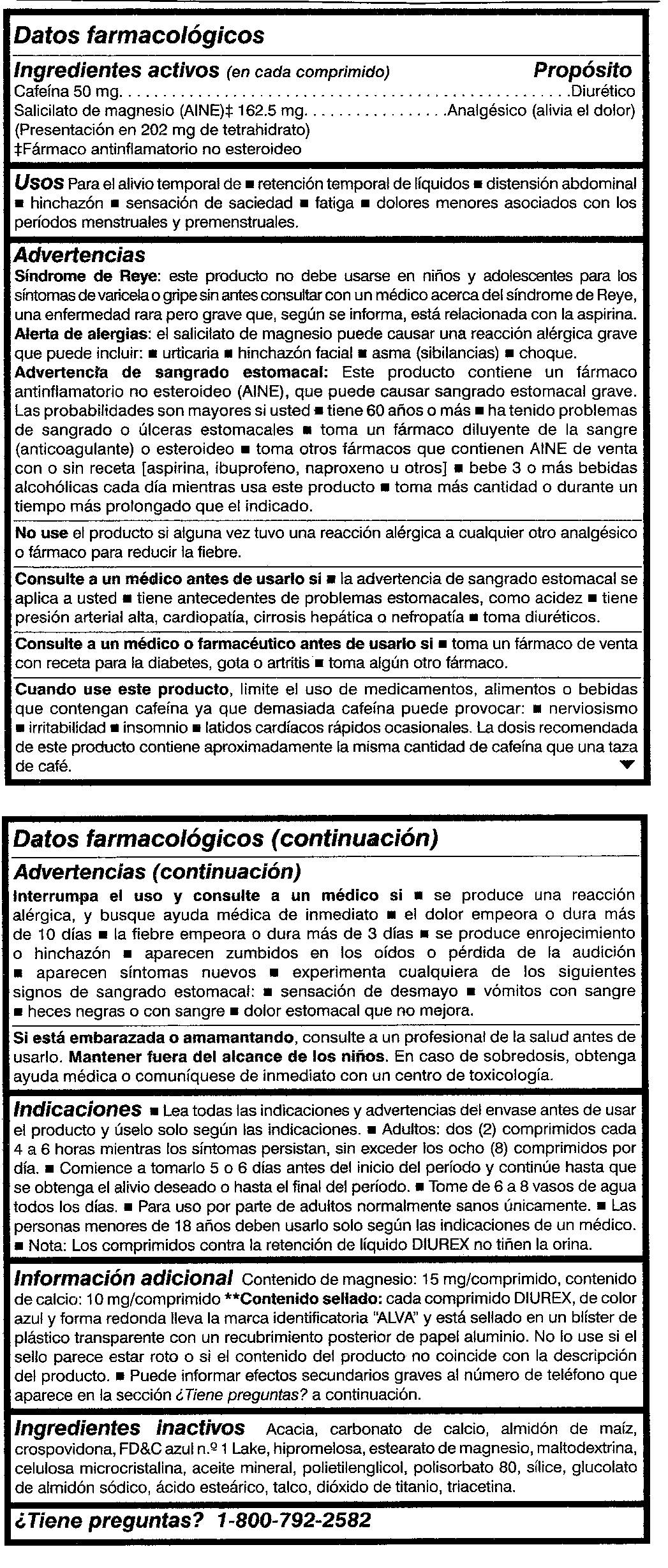 DRUG LABEL: Diurex
NDC: 52389-306 | Form: TABLET, COATED
Manufacturer: Kobayashi Healthcare International, Inc.
Category: otc | Type: HUMAN OTC DRUG LABEL
Date: 20250410

ACTIVE INGREDIENTS: MAGNESIUM SALICYLATE 162.5 mg/1 1; CAFFEINE 50 mg/1 1
INACTIVE INGREDIENTS: ACACIA; CALCIUM CARBONATE; STARCH, CORN; CROSPOVIDONE; FD&C BLUE NO. 1; HYPROMELLOSES; MAGNESIUM STEARATE; MALTODEXTRIN; CELLULOSE, MICROCRYSTALLINE; LIGHT MINERAL OIL; POLYETHYLENE GLYCOL 400; POLYSORBATE 80; SILICON DIOXIDE; SODIUM STARCH GLYCOLATE TYPE A POTATO; STEARIC ACID; TALC; TITANIUM DIOXIDE; TRIACETIN

Diurex Water Pills

Active ingredients (in each pill)

Caffeine, 50 mg

Magnesium Salicylate (NSAID)*, 162.5 mg

(Present as 202 mg of the Tetrahydrate)

*Non-steroidal anti-inflammatory drug

Purpose

Diuretic

Analgesic (pain reliever)

Uses

For temporary relief of

- temporary water retention
- bloat
- swelling
- full feeling
- fatigue
- minor aches and pains

associated with the premenstrual and menstrual periods.

Warnings

Reye's Syndrome: Children and teenagers should not use this product for chicken pox or flu symptoms before a doctor is consulted about Reye's Syndrome, a rare but serious illness reported to be associated with aspirin.

Allergy alert: Magnesium Salicylate may cause a severe allergic reaction which may include:

- hives
- facial swelling
- asthma (wheezing)
- shock

Stomach bleeding warning: This product contains a non-steroidal anti-inflammatory drug (NSAID), which may cause severe stomach bleeding. The chance is higher if you

- are age 60 or older
- have had stomach ulcers or bleeding problems
- take a blood thinning (anticoagulant) or steroid drug
- take other drugs containing prescription or nonprescription NSAIDs [aspirin, ibuprofen, naproxen or others]
- have 3 or more alcoholic drinks every day while using this product
- take more or for a longer time than directed.

Do not use if you have ever had an allergic reaction to any other pain reliever/fever reducer.

Ask a doctor before use if

- stomach bleeding warning applies to you
- you have a history of stomach problems, such as heartburn
- you have high blood pressure, heart disease, liver cirrhosis or kidney disease
- you are taking a diuretic.

Ask a doctor or pharmacist before use if you are

- taking a prescription drug for diabetes, gout or arthritis
- taking any other drug

When using this product, limit the use of caffeine containing medications, foods or beverages because too much caffeine may cause:

- nervousness
- irritability
- sleeplessness
- occasional rapid heart beat

The recommended dose of this product contains about as much caffeine as one cup of coffee.

Stop use and ask a doctor if

- an allergic reaction occurs. Seek medical help right away.
- pain gets worse or lasts more than 10 days.
- fever gets worse or lasts more than 3 days.
- redness or swelling is present.
- ringing in the ears or loss of hearing occurs.
- any new symptoms appear.
- you experience any of the following signs of stomach bleeding:
-
  - feel faint
  - vomit blood
  - have bloody or black stools
  - have stomach pain that does not get better.

PREGNANCY OR BREAST FEEDING

If pregnant or breastfeeding, ask a health professional before use.

Keep out of reach of children. In case of overdose, get medical help or contact a poison control center right away.

Directions

- Read all package directions and warnings before use and use only as directed.
- Adults: Two (2) pills every 4 to 6 hours while symptoms persist, not to exceed eight (8) pills per day.
- Start taking 5 or 6 days before onset of period and continue until desired relief is obtained or end of period.
- Drink 6 to 8 glasses of water daily.
- For use by normally healthy adults only.
- Persons under 18 years of age should use only as directed by a doctor.
- Note: DIUREX Water Pills will not discolor urine.

Other information

Magnesium content: 15 mg/pill, Calcium content: 10 mg/pill **Contents sealed: Each DIUREX blue colored, round shaped pill bears the identifying mark “ALVA" and is sealed in a clear plastic blister with a foil backing. Do not use if seal appears broken or if product contents do not match product description. You may report serious side effects to the phone number provided under Questions? below.

Inactive ingredients

Acacia, calcium carbonate, corn starch, crospovidone, FD&C Blue #1 Lake, hypromellose, magnesium stearate, maltodextrin, microcrystalline cellulose, mineral oil, polyethylene glycol, polysorbate 80, silica, sodium starch glycolate, stearic acid, talc, titanium dioxide, triacetin.

Questions? 1-800-792-2582